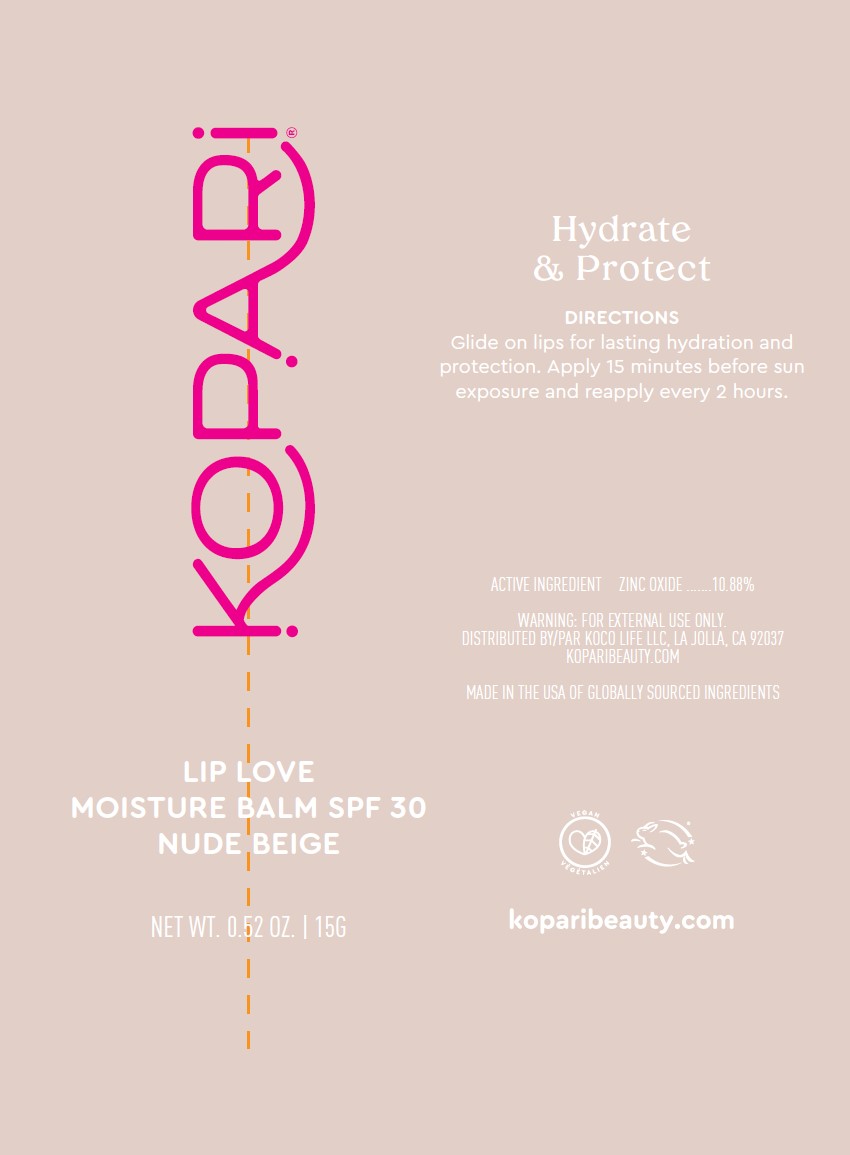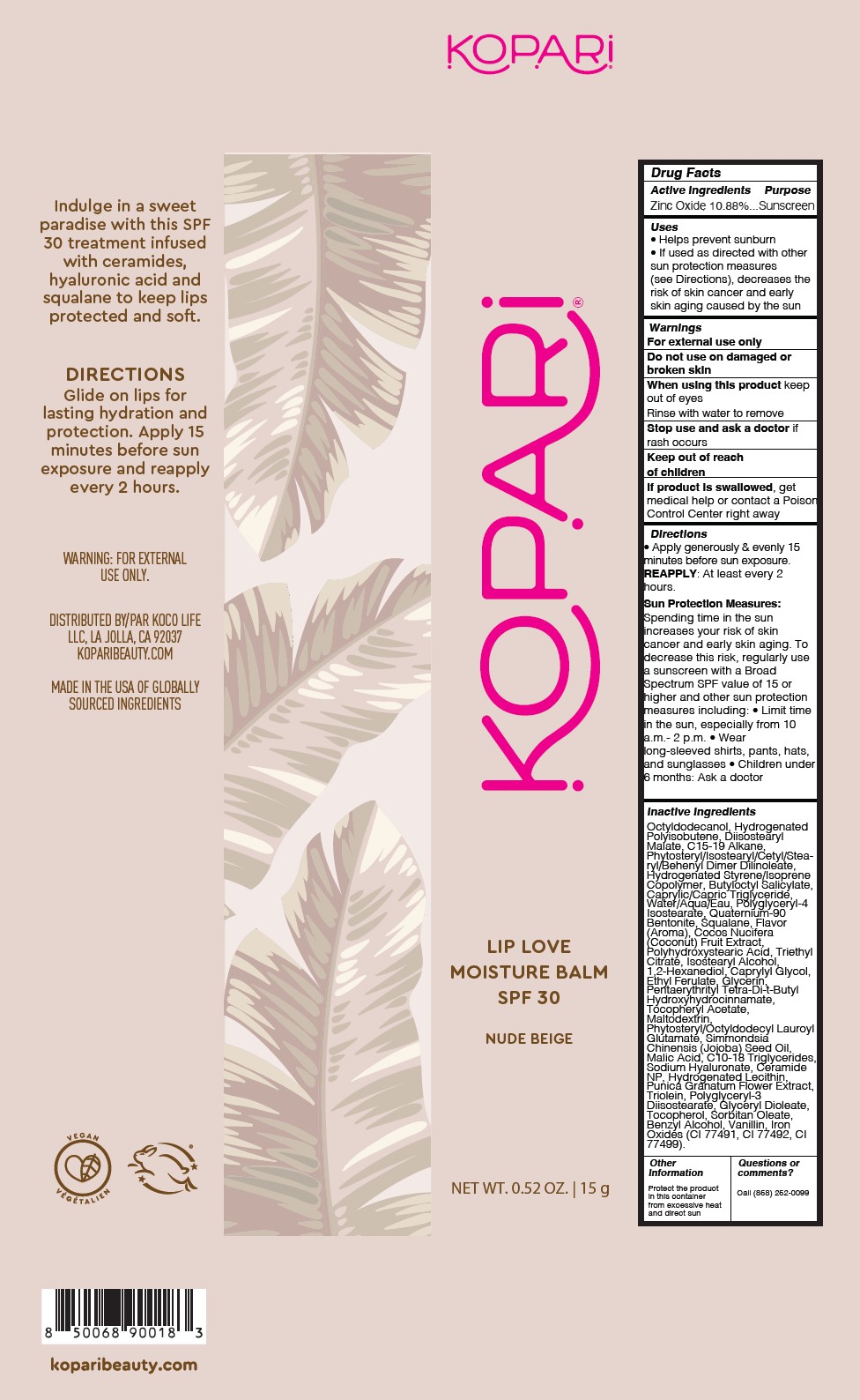 DRUG LABEL: Lip Love Moisture Balm SPF30 - Nude Beige
NDC: 84130-015 | Form: GEL
Manufacturer: Koco Life LLC
Category: otc | Type: HUMAN OTC DRUG LABEL
Date: 20250507

ACTIVE INGREDIENTS: ZINC OXIDE 10.88 g/100 g
INACTIVE INGREDIENTS: TRIETHYL CITRATE; HYDROGENATED SOYBEAN LECITHIN; SORBITAN OLEATE; OCTYLDODECANOL; PHYTOSTERYL/ISOSTEARYL/CETYL/STEARYL/BEHENYL DIMER DILINOLEATE; ISOSTEARYL ALCOHOL; HYDROGENATED POLYISOBUTENE 8; POLYHYDROXYSTEARIC ACID (2300 MW); BENZYL ALCOHOL; CI 77492; POLYGLYCERYL-4 ISOSTEARATE; QUATERNIUM-90 BENTONITE; MALTODEXTRIN; POLYGLYCERYL-3 DIISOSTEARATE; WATER; COCOS NUCIFERA (COCONUT) FRUIT; PHYTOSTERYL/OCTYLDODECYL LAUROYL GLUTAMATE; CAPRYLYL GLYCOL; ETHYL FERULATE; VANILLIN; DIISOSTEARYL MALATE; 1,2-HEXANEDIOL; GLYCERIN; MALIC ACID; CERAMIDE NP; PUNICA GRANATUM FLOWER; TRIOLEIN; PENTAERYTHRITYL TETRA-DI-T-BUTYL HYDROXYHYDROCINNAMATE; JOJOBA OIL; C10-18 TRIGLYCERIDES; CI 77499; C15-19 ALKANE; BUTYLOCTYL SALICYLATE; GLYCERYL DIOLEATE; TOCOPHEROL; CAPRYLIC/CAPRIC TRIGLYCERIDE; SQUALANE; .ALPHA.-TOCOPHEROL ACETATE; SODIUM HYALURONATE; CI 77491

Lip Love Moisture Balm SPF30 - Nude Beige

Active ingredient

Zinc Oxide 10.88%

Purpose

Zinc Oxide 10.88%...Sunscreen

Uses

• Helps prevent sunburn

• If used as directed with othersun protection measures(see Directions), decreases therisk of skin cancer and earlyskin aging caused by the sun

Warnings

For external use only

Do not use on damaged orbroken skin

When using this product keep out of eyes

Rinse with water to remove

Stop use and ask a doctor if rash occurs

Keep out of reachof children
If product is swallowed , get medical help or contact a Poison Control Center right away

Directions

• Apply generously & evenly 15 minutes before sun exposure. REAPPLY: At least every 2 hours.

Sun Protection Measures: Spending time in the sun increases your risk of skin cancer and early skin aging. To decrease this risk, regularly use a sunscreen with a Broad Spectrum SPF value of 15 or higher and other sun protection measures including: • Limit time in the sun, especially from 10 a.m.- 2 p.m. • Wearlong-sleeved shirts, pants, hats, and sunglasses • Children under 6 months: Ask a doctor

Inactive ingredients

Octyldodecanol, Hydrogenated Polyisobutene, Diisostearyl Malate, C15-19 Alkane, Phytosteryl/Isostearyl/Cetyl/Stearyl/Behenyl Dimer Dilinoleate, Hydrogenated Styrene/Isoprene Copolymer, Butyloctyl Salicylate, Caprylic/Capric Triglyceride, Water/Aqua/Eau, Polyglyceryl-4 Isostearate, Quaternium-90 Bentonite, Squalane, Flavor (Aroma), Cocos Nucifera (Coconut) Fruit Extract, Polyhydroxystearic Acid, Triethyl Citrate, Isostearyl Alcohol, 1,2-Hexanediol, Caprylyl Glycol, Ethyl Ferulate, Glycerin, Pentaerythrityl Tetra-Di-t-Butyl Hydroxyhydrocinnamate, Tocopheryl Acetate, Maltodextrin, Phytosteryl/Octyldodecyl Lauroyl Glutamate, Simmondsia Chinensis (Jojoba) Seed Oil, Malic Acid, C10-18 Triglycerides, Sodium Hyaluronate, Ceramide NP, Hydrogenated Lecithin, Punica Granatum Flower Extract, Triolein, Polyglyceryl-3 Diisostearate, Glyceryl Dioleate, Tocopherol, Sorbitan Oleate, Benzyl Alcohol, Vanillin, Iron Oxides (CI 77491, CI 77492, CI 77499)

Other information

Protect the product in this container from excessive heat and direct sun

Questions or comments?

Call (858) 252-0099